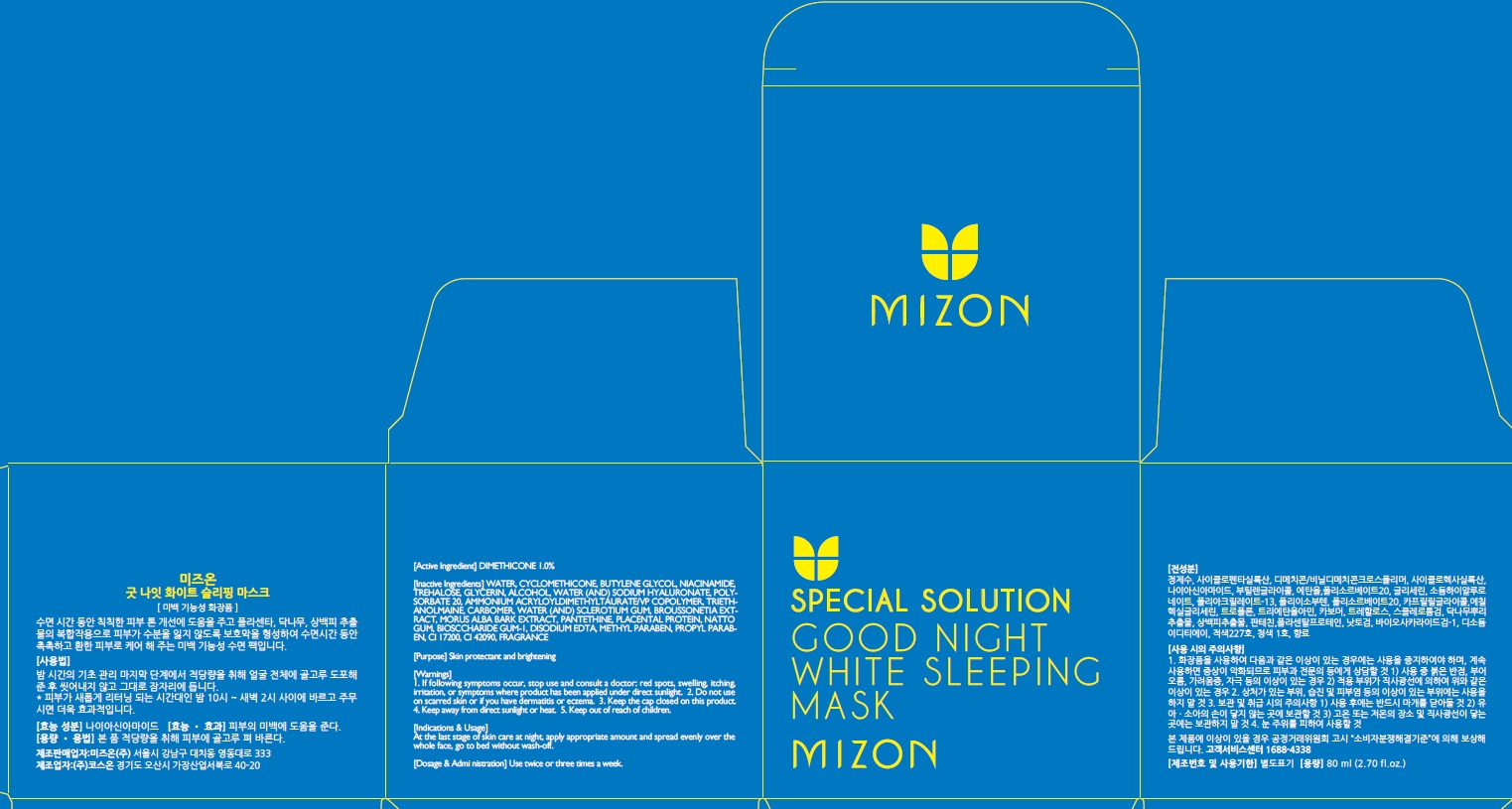 DRUG LABEL: MIZON GOOD NIGHT WHITE SLEEPING MASK
NDC: 57718-100 | Form: CREAM
Manufacturer: MIZON CO., LTD.
Category: otc | Type: HUMAN OTC DRUG LABEL
Date: 20160323

ACTIVE INGREDIENTS: DIMETHICONE 0.8 g/80 mL
INACTIVE INGREDIENTS: WATER; NIACINAMIDE

ACTIVE INGREDIENT

Active Ingredient: DIMETHICONE 1.0%

INACTIVE INGREDIENT

Inactive Ingredients: WATER, CYCLOMETHICONE, BUTYLENE GLYCOL, NIACINAMIDE, TREHALOSE, GLYCERIN, ALCOHOL, WATER (AND) SODIUM HYALURONATE, POLYSORBATE 20, AMMONIUM ACRYLOYLDIMETHYLTAURATE/VP COPOLYMER, TRIETHANOLMAINE, CARBOMER, WATER (AND) SCLEROTIUM GUM, BROUSSONETIA EXTRACT, MORUS ALBA BARK EXTRACT, PANTETHINE, PLACENTAL PROTEIN, NATTO GUM, BIOSCCHARIDE GUM-1, DISODIUM EDTA, METHYL PARABEN, PROPYL PARABEN, CI 17200, CI 42090, FRAGRANCE

PURPOSE

Purpose: Skin protectant and brightening

WARNINGS

Warnings: 1. If following symptoms occur, stop use and consult a doctor: red spots, swelling, itching, irritation, or symptoms where product has been applied under direct sunlight. 2. Do not use on scarred skin or if you have dermatitis or eczema. 3. Keep the cap closed on this product. 4. Keep away from direct sunlight or heat. 5. Keep out of reach of children.

KEEP OUT OF REACH OF CHILDREN

INDICATIONS & USAGE

Indications & Usage: At the last stage of skin care at night, apply appropriate amount and spread evenly over the whole face, go to bed without wash-off.

DOSAGE & ADMINISTRATION

Dosage & Administration: Use twice or three times a week.